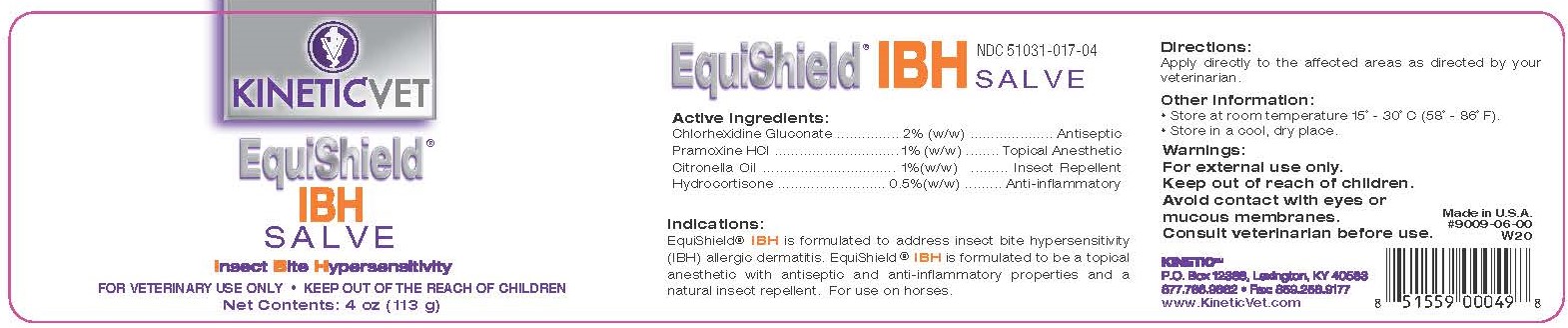 DRUG LABEL: EquiShield IBH Salve
NDC: 51031-017 | Form: SALVE
Manufacturer: Kinetic Technologies, LLC
Category: animal | Type: OTC ANIMAL DRUG LABEL
Date: 20231127

ACTIVE INGREDIENTS: CHLORHEXIDINE GLUCONATE 2 g/100 g; PRAMOXINE HYDROCHLORIDE 1 g/100 g; CITRONELLA OIL 1 g/100 g; HYDROCORTISONE 0.5 g/100 g

EquiShield IBH Salve

Active Ingredients:

Chlorhexidine Gluconate........2% (w/w)....................Antiseptic

Pramoxine HCL.....................1% (w/w).........Topical Anesthetic

Citronella Oil....................... 1% (w/w)............Insect Repellent

Hydrocortisone .................0.5% (w/w).........Anti-Inflammatory

Indications:

EquiShield® IBH Salve is formulated to address insect bite hypersensitivity (IBH) allergic dermatitis. EquiShield® IBH is formulated to be a topical anesthetic with antiseptic and anti-inflammatory properties and a natural insect repellant. For use on horses.

Directions:

Apply directly to the affected areas as directed by your veterinarian.

Warnings:

For external use only.

Keep out of reach of children.

Avoid contact with eyes or mucous membranes.

Consult your veterinarian before use.

Other Information:

• Store at room temperature 15˚ - 30˚C (58˚ - 86˚F).
• Store in a cool, dry place.

Made in U.S.A.

KINETIC™

P.O. Box 12388, Lexington, KY 40583

877.786.9882 • Fax: 859.258.9177

www.KineticVet.com

KINETIC™VET

EquiShield® IBH SALVE

Insect Bite Hypersensitivity

FOR VETERINARY USE ONLY • KEEP OUT OF THE REACH OF CHILDREN

Net Contents: 4 oz (113 g)